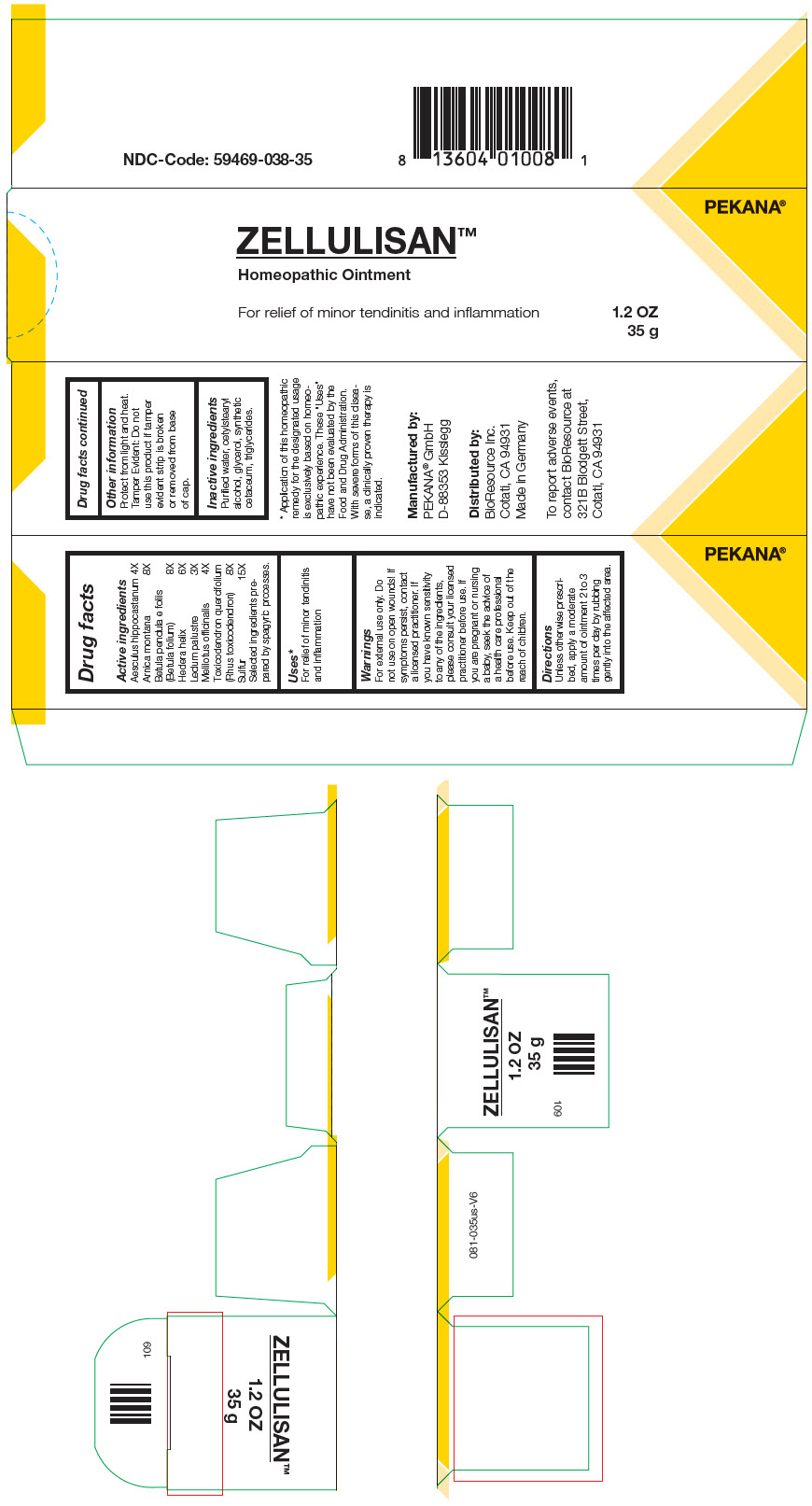 DRUG LABEL: Zellulisan
NDC: 59469-038 | Form: OINTMENT
Manufacturer: Pekana-Naturheilmittel GmbH
Category: homeopathic | Type: HUMAN OTC DRUG LABEL
Date: 20221221

ACTIVE INGREDIENTS: horse chestnut 4 [hp_X]/35 g; ARNICA MONTANA WHOLE 8 [hp_X]/35 g; betula pendula leaf 8 [hp_X]/35 g; hedera helix flowering twig 6 [hp_X]/35 g; RHODODENDRON TOMENTOSUM LEAFY TWIG 3 [hp_X]/35 g; melilotus officinalis top 4 [hp_X]/35 g; toxicodendron pubescens leaf 8 [hp_X]/35 g; sulfur 15 [hp_X]/35 g
INACTIVE INGREDIENTS: water; cetostearyl alcohol; glycerin; medium-chain triglycerides; cetyl esters wax

ZELLULISAN™
spag.
Homeopathic
Ointment

Drug facts

Active ingredients
Aesculus hippocastanum | 4X
Arnica montana | 8X
Betula pendula e foliis (Betula folium) | 8X
Hedera helix | 6X
Ledum palustre | 3X
Melilotus officinalis | 4X
Toxicodendron quercifolium (Rhus toxicodendron) | 8X
Sulfur | 15X

Selected ingredients prepared by spagyric processes.

Uses [Application of this homeopathic remedy for the designated usage is exclusively based on homeopathic experience. These "Uses" have not been evaluated by the Food and Drug Administration. With severe forms of this disease, a clinically proven therapy is indicated.]

PURPOSE

For relief of minor tendinitis and inflammation

Warnings

For external use only. Do not use on open wounds! If symptoms persist, contact a licensed practitioner. If you have known sensitivity to any of the ingredients, please consult your licensed practitioner before use. If you are pregnant or nursing a baby, seek the advice of a health care professional before use.

Keep out of the reach of children.

Directions

Unless otherwise prescribed, apply a moderate amount of ointment 2 to 3 times per day by rubbing gently into the affected area.

Other information

Protect from light and heat.

Tamper Evident

Do not use this product if tamper evident strip is broken or removed from base of cap.

Inactive ingredients

Purified water, cetylstearyl alcohol, glycerol, synthetic cetaceum, triglycerides.

Manufactured by:
PEKANA® GmbH
D-88353 Kisslegg

Distributed by:
BioResource Inc.
Cotati, CA 94931

PRINCIPAL DISPLAY PANEL - 35 g Tube Carton

PEKANA®

ZELLULISAN™
Homeopathic Ointment

For relief of minor tendinitis and inflammation

1.2 OZ
35 g